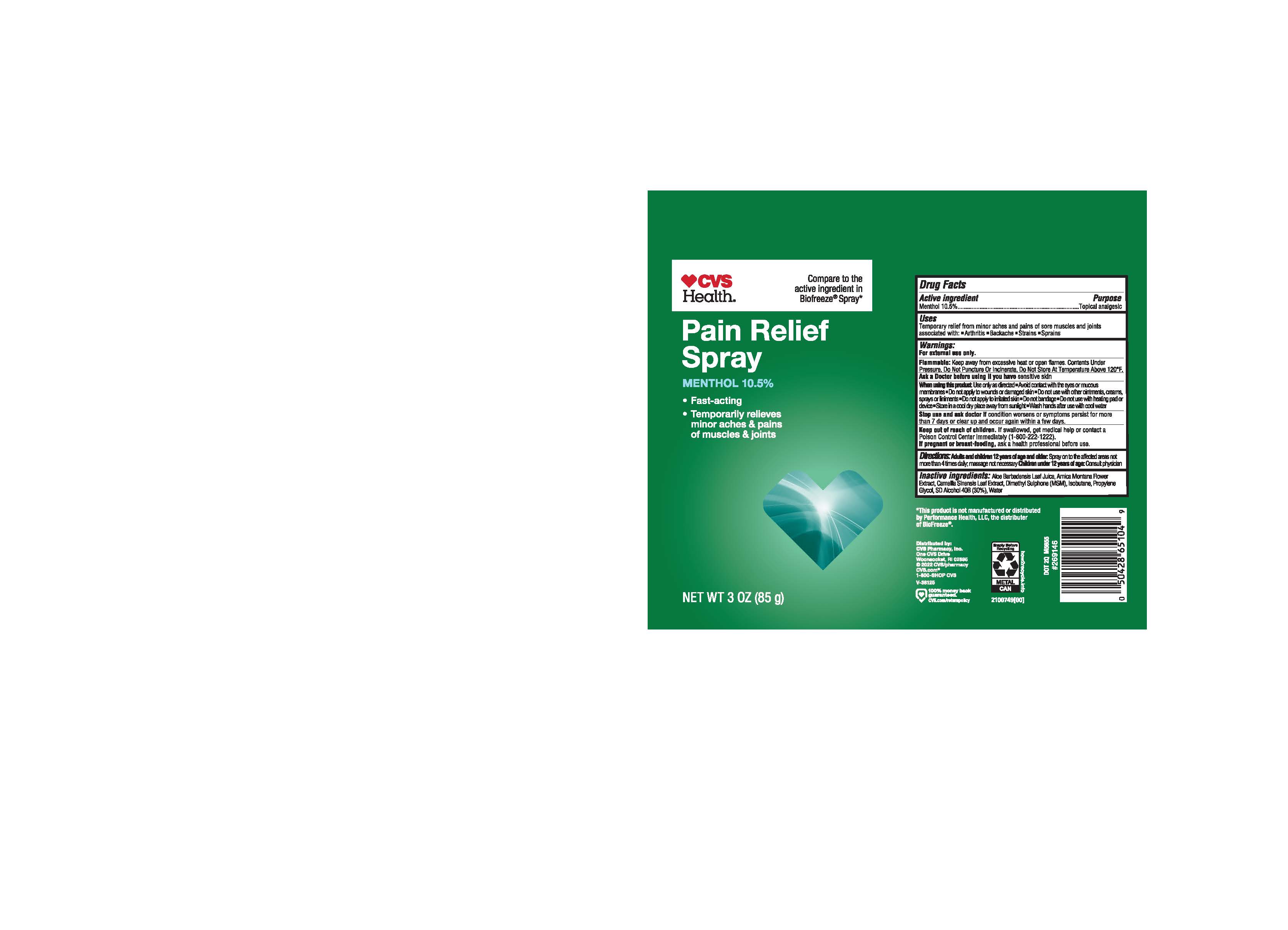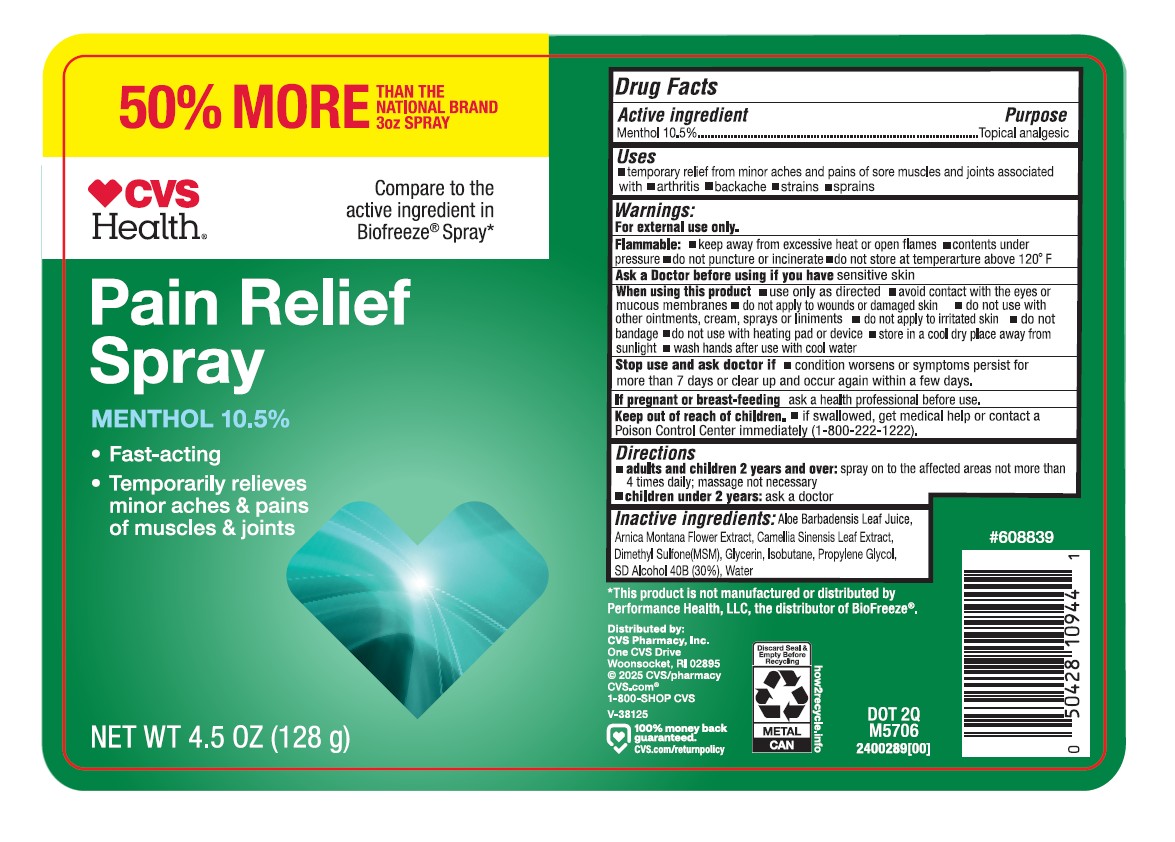 DRUG LABEL: CVS Pain Relief
NDC: 51316-996 | Form: SPRAY
Manufacturer: CVS
Category: otc | Type: HUMAN OTC DRUG LABEL
Date: 20250331

ACTIVE INGREDIENTS: MENTHOL 10.5 g/100 g
INACTIVE INGREDIENTS: GREEN TEA LEAF; WATER; DIMETHYL SULFONE; DEHYDRATED ALCOHOL; PROPYLENE GLYCOL; ISOBUTANE; GLYCERIN; ALOE VERA LEAF; ARNICA MONTANA

CVS Pain Relief Spray

ACTIVE INGREDIENT

Menthol 10.5%

PURPOSE

Topical analgesic

INDICATIONS AND USAGE

Temporary relief from minor aches of sore muscles and joints associated with:

Arthritis

Backache

Strains

Sprains

WARNINGS

For external use only

Flammable: Keep away from excessive heat or open flames. Contents Under Pressure.

Do Not Puncture Or Incinerate

Do Not Store At Temperature Above 120°F

Ask a Doctor before using if you have sensitive skin

When using this product:

Use only as directed

Avoid contact with eyes or mucous membranes

Do not apply to wounds or damaged skin

Do not use with other ointments, creams, sprays or liniments

Do not apply to irritated skin

Do not bandage

Do not use with heating pad or device

Store in a cool dry place away from sunlight

Wash hands after use with cool water

Stop use and ask doctor if condition worsens or symptoms persist for more than 7 days or clear up and occur again within a few days

KEEP OUT OF REACH OF CHILDREN

If swallowed, get medical help or contact a Poison Control Center immediately (1-800-222-1222)

PREGNANCY OR BREAST FEEDING

If pregnant or breast-feeding, ask a health professional before use.

DOSAGE AND ADMINISTRATION

Adults and children 12 years of age and older: Spray on to the affected areas not more than 4 times daily; message not necessary

Children under 12 years of age: Consult physician

INACTIVE INGREDIENT

Aloe Barbadensis leaf Juice, Arnica Montana Flower Extract, Camellia Sinensis Leaf Extract, Dimethyl Sulphone (MSM), Isobutane, Propylene Glycol, SD Alcohol 40 B (30%), Water